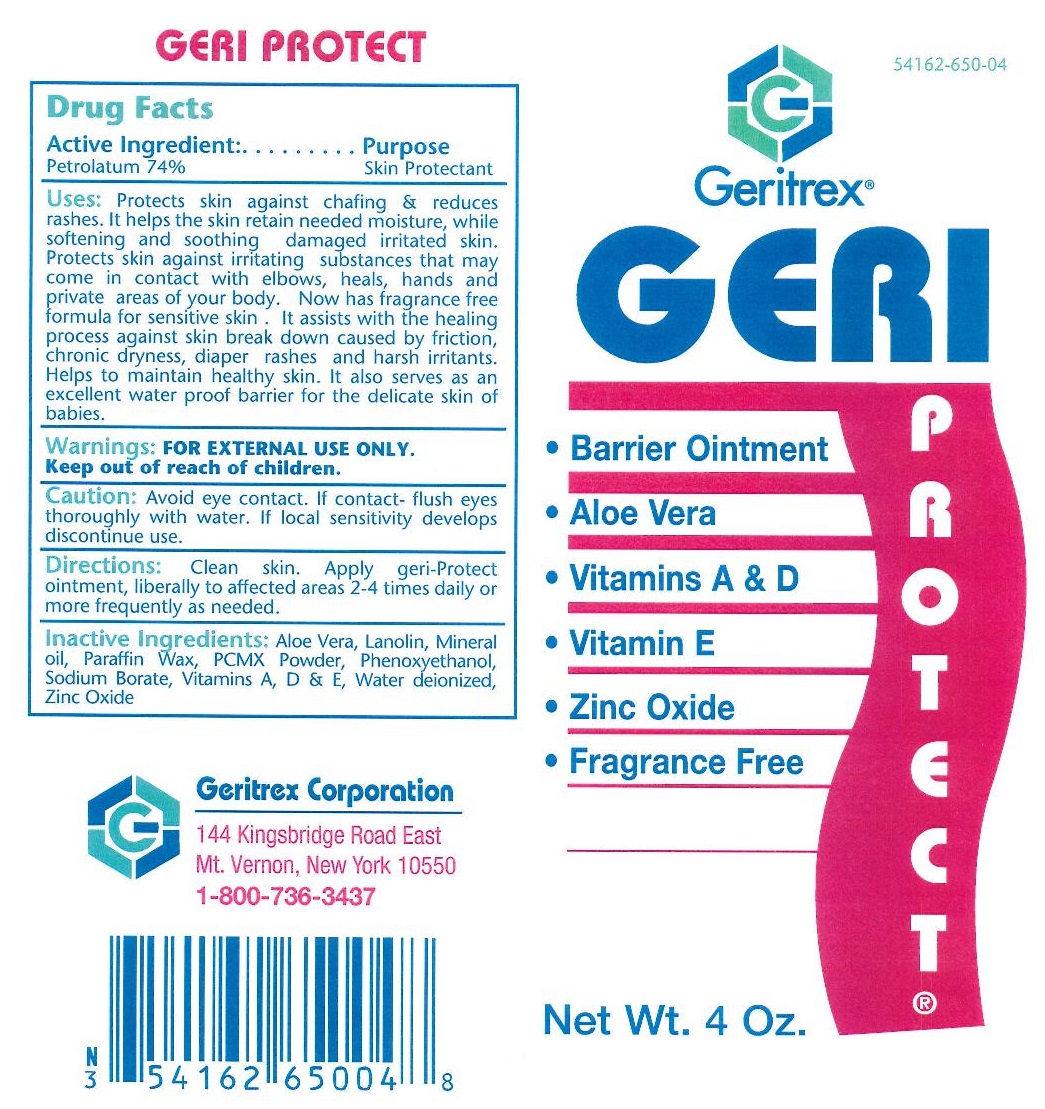 DRUG LABEL: Geri Protect
NDC: 54162-650 | Form: OINTMENT
Manufacturer: Geritrex LLC
Category: otc | Type: HUMAN OTC DRUG LABEL
Date: 20151229

ACTIVE INGREDIENTS: PETROLATUM 87.32 g/118 g
INACTIVE INGREDIENTS: ALOE VERA LEAF; LANOLIN; MINERAL OIL; PARAFFIN; PHENOXYETHANOL; SODIUM BORATE; VITAMIN A; VITAMIN D; WATER; ZINC OXIDE; ALPHA-TOCOPHEROL; CHLOROXYLENOL

Geri Protect

Active Ingredient:

Petrolatum 74%

Purpose

Skin Protectant

WARNINGS

WARNING: FOR EXTERNAL USE ONLY

Keep out of reach of children

WARNINGS AND PRECAUTIONS

Caution: Avoid eye contact. If contact - flush eyes thoroughly with water. If local sensitivity develops discontinue use.

DOSAGE AND ADMINISTRATION

Directions: Clean skin. Apply geri-protect ointment, liberally to affected area 2-4 times daily or more frequently as needed.

INACTIVE INGREDIENT

Inactive Ingredients: Aloe vera, lanolin, mineral oil, Paraffin wax, PCMX Powder, Phenoxyethanol, Sodium Borate, Vitamins A, D, and E, water deionized, Zinc Oxide